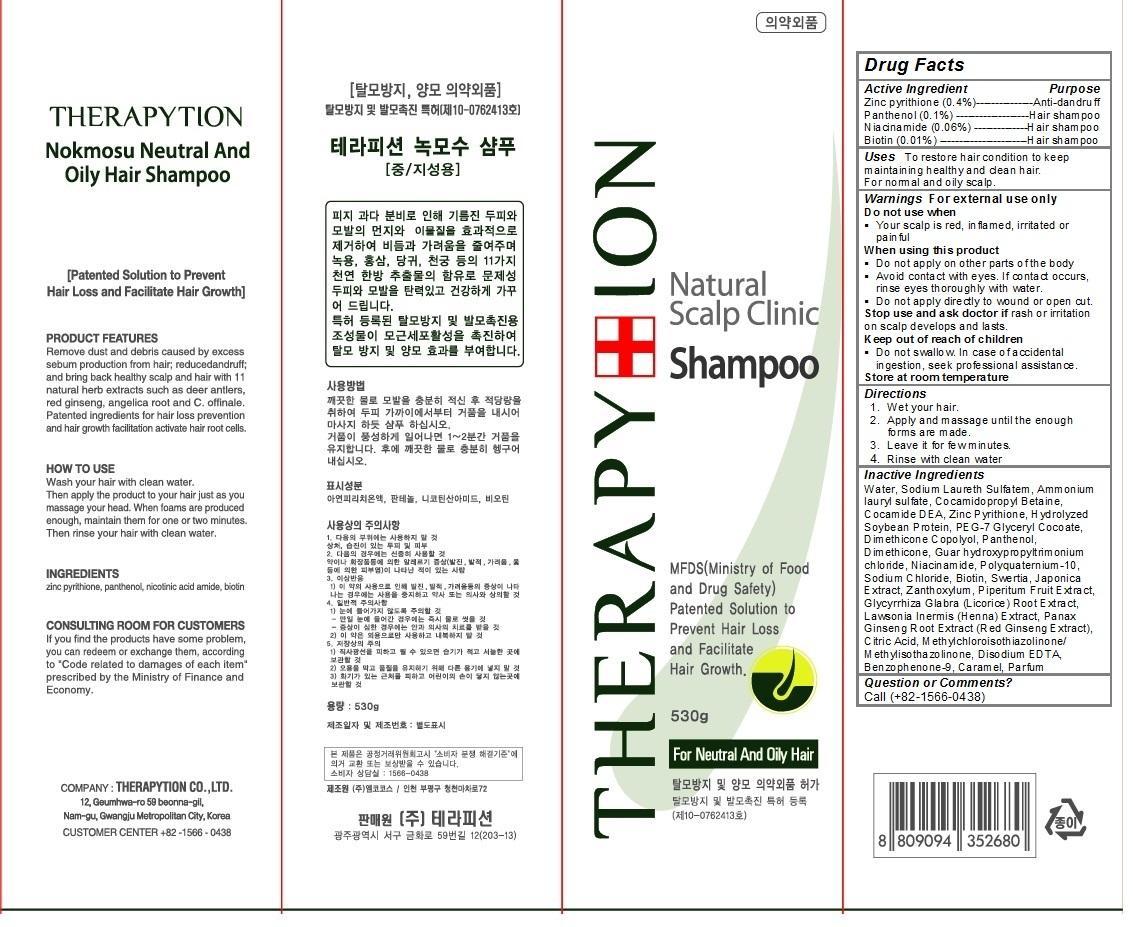 DRUG LABEL: Therapytion Nokmosu Neutral and oily Hair
NDC: 63214-102 | Form: SHAMPOO
Manufacturer: Therapytion Co., Ltd.
Category: otc | Type: HUMAN OTC DRUG LABEL
Date: 20140429

ACTIVE INGREDIENTS: PYRITHIONE ZINC 2.1 g/530 g; PANTHENOL 0.5 g/530 g; NIACINAMIDE 0.3 g/530 g; BIOTIN 0.06 g/530 g
INACTIVE INGREDIENTS: Water; Sodium Laureth Sulfate; Ammonium lauryl sulfate; Cocamidopropyl Betaine; PEG-6 COCAMIDE; SOYBEAN; PEG-7 Glyceryl Cocoate; DIMETHICONE; Sodium Chloride; SWERTIA JAPONICA; GLYCYRRHIZA GLABRA WHOLE; PANAX GINSENG ROOT OIL; CITRIC ACID ACETATE; DISODIUM EDTA-COPPER; Benzophenone-9; Caramel

Therapytion Nokmosu Neutral and oily Hair shampoo